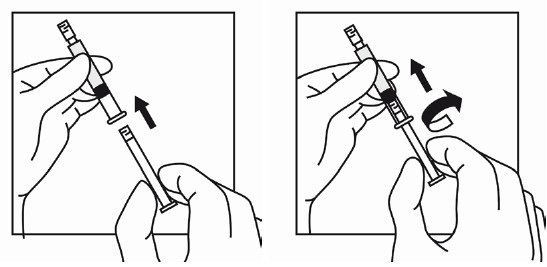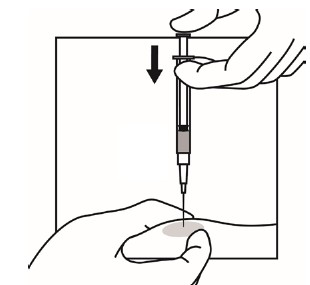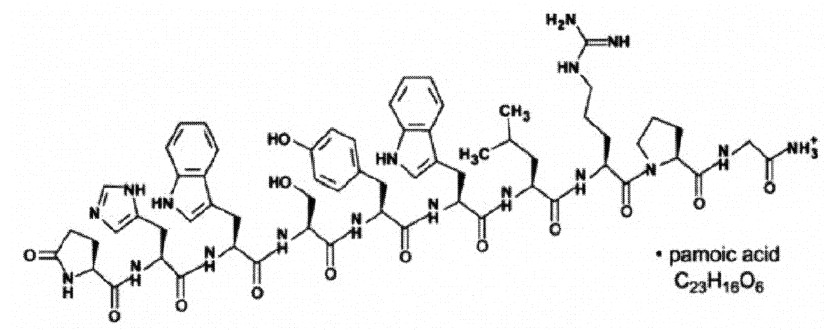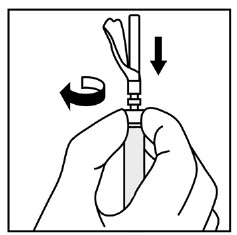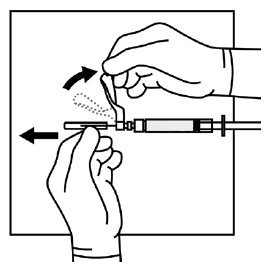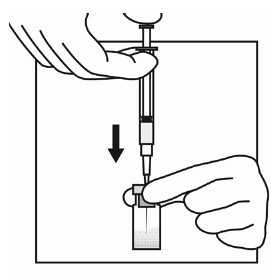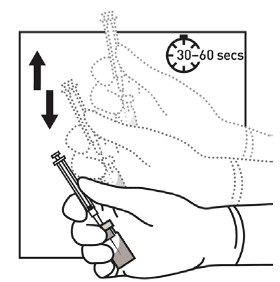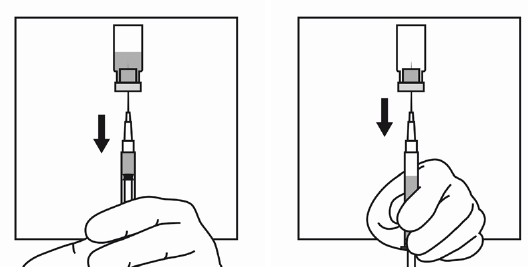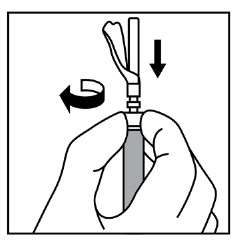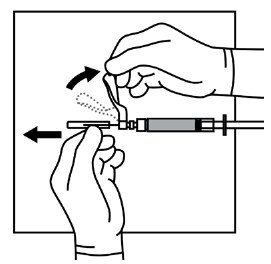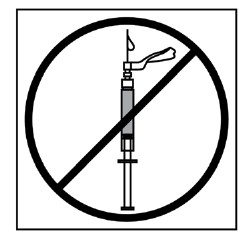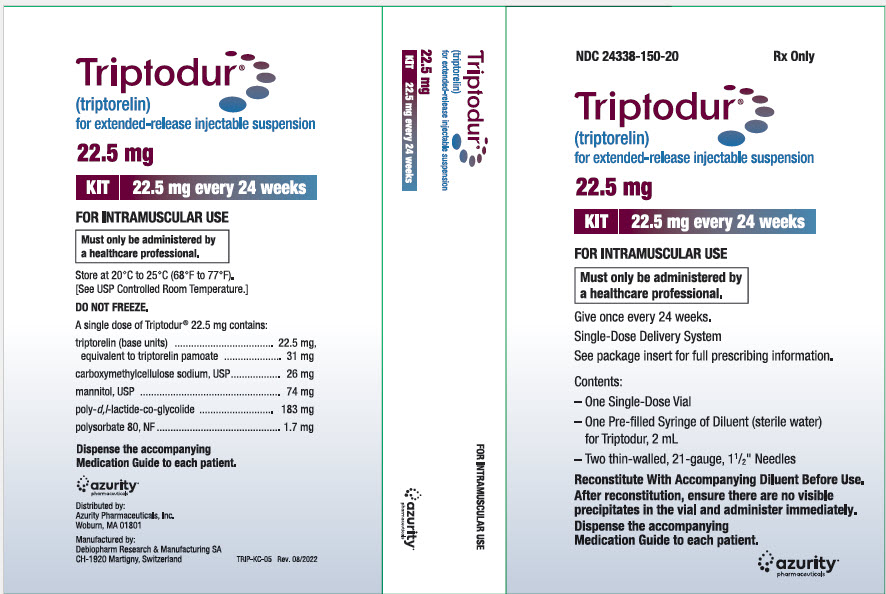 DRUG LABEL: TRIPTODUR
NDC: 24338-150 | Form: KIT | Route: INTRAMUSCULAR
Manufacturer: Azurity Pharmaceuticals, Inc.
Category: prescription | Type: Human Prescription Drug Label
Date: 20250914

ACTIVE INGREDIENTS: TRIPTORELIN 22.5 mg/2 mL
INACTIVE INGREDIENTS: POLY(DL-LACTIC-CO-GLYCOLIC ACID), (50:50; 12000 MW); MANNITOL; CARBOXYMETHYLCELLULOSE SODIUM, UNSPECIFIED; POLYSORBATE 80; WATER

HIGHLIGHTS OF PRESCRIBING INFORMATION

These highlights do not include all the information needed to use TRIPTODUR ®safely and effectively. See full prescribing information for TRIPTODUR.
TRIPTODUR (triptorelin) for extended-release injectable suspension, for intramuscular use
Initial U.S. Approval: 2000

RECENT MAJOR CHANGES

Warnings and Precautions, Severe Cutaneous Adverse Reactions (5.4) 09/2025

1 INDICATIONS AND USAGE

TRIPTODUR is a gonadotropin releasing hormone (GnRH) agonist indicated for the treatment of pediatric patients 2 years and older with central precocious puberty. (1)

2 DOSAGE AND ADMINISTRATION

- Must only be administered by a healthcare provider. (2.1)
- Administer TRIPTODUR as a single intramuscular injection of 22.5 mg once every 24 weeks. (2.1)
- Monitor response with LH levels after a GnRH or GnRH agonist stimulation test, basal LH, or serum concentration of sex steroid levels beginning 1 to 2 months following initiation of therapy, during therapy as necessary to confirm maintenance of efficacy, and with each subsequent dose. (2.2)
- Measure height every 3-6 months and monitor bone age periodically. (2.2)
- See FPI for complete reconstitution and administration instructions. (2.3)
  - Once TRIPTODUR is mixed, proceed to the next steps and administer without delay. (2.3)
  - The injection of the suspension should be performed rapidly and in a steady and uninterrupted manner in order to avoid any potential blockage of the needle. (2.3)

3 DOSAGE FORMS AND STRENGTHS

For extended-release injectable suspension: 22.5 mg of triptorelin as a powder cake for reconstitution with the co-packaged 2 mL of diluent Sterile Water for Injection. (3)

4 CONTRAINDICATIONS

- Hypersensitivity reactions (4)
- Pregnancy (4, 8.1)

5 WARNINGS AND PRECAUTIONS

- Initial Rise of Gonadotropins and Sex Steroid Levels: An increase in clinical signs and symptoms of puberty may be observed during the first 2-4 weeks of therapy since gonadotropins and sex steroids rise above baseline because of the initial stimulatory effect of the drug. (5.1)
- Psychiatric events: Have been reported in patients taking GnRH agonists. Events include emotional lability, such as crying, irritability, impatience, anger, and aggression. Monitor for development or worsening of psychiatric symptoms. (5.2)
- Convulsions: Have been observed in patients with or without a history of seizures, epilepsy, cerebrovascular disorders, central nervous system anomalies or tumors, and in patients on concomitant medications that have been associated with convulsions. (5.3)
- Severe Cutaneous Adverse Reactions (SCARs): Have been reported in patients receiving GnRH agonists, including triptorelin products. Interrupt TRIPTODUR if signs or symptoms of SCARs develop. Permanently discontinue TRIPTODUR if a SCAR is confirmed. (5.4)
- Pseudotumor Cerebri (Idiopathic Intracranial Hypertension): Have been reported in pediatric patients receiving GnRH agonists, including triptorelin. Monitor patients for headache, papilledema, and blurred vision. (5.5)

6 ADVERSE REACTIONS

In clinical trials for TRIPTODUR, the most common adverse reactions (≥4.5%) are injection site reactions, menstrual (vaginal) bleeding, hot flush, headache, cough, and infections (bronchitis, gastroenteritis, influenza, nasopharyngitis, otitis externa, pharyngitis, sinusitis, and upper respiratory tract infection). (6.1)

To report SUSPECTED ADVERSE REACTIONS, contact Azurity Pharmaceuticals, Inc. at 1-800-461-7449 or FDA at 1-800-FDA-1088 or www.fda.gov/medwatch.

FULL PRESCRIBING INFORMATION

1 INDICATIONS AND USAGE

TRIPTODUR is indicated for the treatment of pediatric patients 2 years of age and older with central precocious puberty (CPP).

2 DOSAGE AND ADMINISTRATION

2.1 Dosing Information

TRIPTODUR must only be administered by a healthcare provider.

The dosage of TRIPTODUR is 22.5 mg reconstituted with accompanying diluent (Sterile Water) 2 mL, and administered as a single intramuscular injection once every 24 weeks.

TRIPTODUR treatment should be discontinued at the appropriate age of onset of puberty at the discretion of the physician.

2.2 Monitoring

Monitor response to TRIPTODUR with LH levels after a GnRH or GnRH agonist stimulation test, basal LH, or serum concentration of sex steroid levels beginning 1 to 2 months following initiation of therapy, during therapy as necessary to confirm maintenance of efficacy, and with each subsequent dose.

Measure height (for calculation of growth rate) every 3-6 months and monitor bone age periodically.

Noncompliance with drug regimen or inadequate dosing may result in inadequate control of the pubertal process with gonadotropins and/or sex steroids increasing above prepubertal levels. If the dose of TRIPTODUR is not adequate switching to an alternative GnRH agonist for the treatment of CPP with the ability for dose adjustment may be necessary.

2.3 Reconstitution and Administration Instructions

Read these instructions completely before you begin.

• Triptodur suspension will sediment very quickly and should be injected immediately after reconstitution in accordance with the detailed instructions below.

• If the sequence of steps to prepare the suspension is interrupted and/or the vial is put aside, the suspension will start to separate into diluent and microgranules.

• To minimize the risk of needle blockage during the injection, ensure that the preparation of the injection is not interrupted and/or the mixed suspension syringe is not put aside because the suspension will sediment quickly.

1. Use appropriate aseptic technique for preparation and administration.
2. Screw the plunger rod into the barrel end of the prefilled sterile water diluent syringe.

3. To remove the cap, twist counterclockwise to separate from the Luer lock on the syringe barrel.
4. Firmly attach one of the 21-gauge sterile safety needles onto the prefilled sterile
water diluent syringe with a push and clockwise twist. This 21-gauge needle will only be used for reconstitution of the product.

a. Remove the plastic Flip-off from the vial. Disinfect the visible part of the stopper
b. Pull back on the safety cover towards the syringe and away from the 21-gauge needle. Then pull the clear needle shield off.

5. Insert the 21-gauge needle through the stopper. Inject the Sterile Water diluent into the vial, ensuring the diluent rinses the sides of the vial. Do not release the plunger rod.

6. If the syringe plunger is not maintained in position, it will naturally withdraw product into the syringe. Thoroughly mix the vial with agitation for 30 to 60 seconds, ensuring the diluent rinses the sides of the vial.

7. Before moving on to the next step, check visually that the suspension appears milky and homogeneous without any visible aggregates or precipitates.
a. If the suspension DOES NOT appear milky and homogeneous without any visible aggregates or precipitates, continue with the agitation. An up and down agitation can also be used to help eliminate aggregates or precipitates. The complete and homogeneous (milky) suspension of the product may require up to 60 seconds of agitation.
Important: Once mixed, proceed to the next steps and administer without delay.
8. The suspension will sediment very quickly so it is imperative to withdraw the suspension into the syringe directly after suspending the product in the vial.
9. Invert the vial and move back the syringe in order to position the end of the 21-gauge needle very near the level of the stopper, making sure the needle lumen is still completely in the vial.
10. Pull back the plunger rod slowly to withdraw the reconstituted product into the syringe, withdrawing as much of the reconstituted product into the syringe as possible. Move the tip of the needle at the level of the stopper so as to be able to withdraw a maximum amount of suspension.

11. Withdraw the needle from the vial and push the safety cover forward toward the needle until you hear and/or feel it lock. Then remove the first 21-gauge needle by grasping the needle hub to disconnect the needle from the syringe and discard it. This (first) 21-gauge needle will no longer be used.

12. Firmly attach the second sterile needle onto the syringe with a push and clockwise twist and pull back the safety cover towards the syringe. This 21-gauge needle will be used for administration. Triptodur must only be administered with a thin-wall 21 -gauge needle.

13. Do not prime the needle. Inspect the suspension visually for particulate matter and discoloration.

a. If the suspension does not appear milky and homogeneous, continue with an up and down agitation.
b. If the suspension appears milky and homogeneous without visible aggregates or precipitates, administer the suspension immediately.
14. Inject the patient intramuscularly, preferably in either buttock or thigh using the entire contents of the syringe. The injection of the suspension should be performed rapidly and in a steady and uninterrupted manner in order to avoid any potential blockage of the needle.

15. After administering the injection, immediately activate the safety cover:
a. Center your thumb or forefinger on the textured finger pad area of the safety cover and push it forward over the needle until you hear or feel it lock.
b. Use the one-handed technique and activate the mechanism away from yourself and others.
c. Immediately discard the syringe assembly into a suitable sharps container.

3 DOSAGE FORMS AND STRENGTHS

For extended-release injectable suspension: 22.5 mg of triptorelin as a lyophilized white to slightly yellow powder cake in a single-dose vial for reconstitution with the co-packaged 2 mL of diluent (Sterile Water) for Injection.

4 CONTRAINDICATIONS

- Hypersensitivity: TRIPTODUR is contraindicated in individuals with a known hypersensitivity to triptorelin, any other component of the product, or other GnRH agonists or GnRH [see Adverse Reactions (6.2)] .
- Pregnancy: TRIPTODUR may cause fetal harm [see Use in Specific Populations (8.1)] .

5 WARNINGS AND PRECAUTIONS

5.1 Initial Rise of Gonadotropins and Sex Steroid Levels

During the early phase of initial therapy or after subsequent doses, gonadotropins and sex steroids may rise above baseline because of a transient stimulatory effect of the drug [see Clinical Pharmacology (12.2)] . Therefore, a transient increase in clinical signs and symptoms of puberty, including vaginal bleeding, may be observed during the first weeks of therapy or after subsequent doses.

5.2 Psychiatric Events

Psychiatric events have been reported in patients taking GnRH agonists, including triptorelin. Post-marketing reports with this class of drugs include symptoms of emotional lability, such as crying, irritability, impatience, anger, and aggression. Monitor for development or worsening of psychiatric symptoms during treatment with TRIPTODUR [see Adverse Reactions (6)] .

5.3 Convulsions

Post-marketing reports of convulsions have been observed in patients receiving GnRH agonists, including triptorelin. These included patients with a history of seizures, epilepsy, cerebrovascular disorders, central nervous system anomalies or tumors, and patients on concomitant medications that have been associated with convulsions such as bupropion and SSRIs. Convulsions have also been reported in patients in the absence of any of the conditions mentioned above [ see Adverse Reactions (6)].

5.4 Severe Cutaneous Adverse Reactions (SCARs)

Severe cutaneous adverse reactions (SCARs) have been reported in patients receiving GnRH agonists, including triptorelin products [see Adverse Reactions (6.2)]. These reactions include Stevens-Johnson syndrome/toxic epidermal necrolysis (SJS/TEN), drug reaction with eosinophilia and systemic symptoms (DRESS), and acute generalized exanthematous pustulosis (AGEP), including cases with visceral involvement and/or requiring skin grafts.
Monitor patients for signs and symptoms of SCARs such as fever, flu-like symptoms, mucosal lesions, progressive skin rash or lymphadenopathy. Advise patients and caregivers of the signs and symptoms of SCARs.
If a SCAR is suspected, interrupt TRIPTODUR. Consult a healthcare provider with expertise in the diagnosis and management of SCARS. If a diagnosis is confirmed permanently discontinue TRIPTODUR.

5.5 Pseudotumor Cerebri (Idiopathic Intracranial Hypertension)

Pseudotumor cerebri (idiopathic intracranial hypertension) has been reported in pediatric patients receiving GnRH agonists, including triptorelin. Monitor patients for signs and symptoms of pseudotumor cerebri, including headache, papilledema, blurred vision, diplopia, loss of vision, pain behind the eye or pain with eye movement, tinnitus, dizziness, and nausea.

6 ADVERSE REACTIONS

The following serious adverse reactions are described here and elsewhere in the label:

- Initial Rise of Gonadotropins and Sex Steroid Levels [see Warnings and Precautions (5.1)]
- Psychiatric Events [see Warnings and Precautions (5.2)]
- Convulsions [see Warnings and Precautions (5.3)]
- Severe Cutaneous Adverse Reactions [see Warnings and Precautions (5.4)]
- Pseudotumor Cerebri (Idiopathic Intracranial Hypertension) [see Warnings and Precautions (5.5)]

6.1 Clinical Trials Experience

Because clinical trials are conducted under widely varying conditions, adverse reaction rates observed in the clinical trials of a drug cannot be directly compared to rates in the clinical trials of another drug and may not reflect the rates observed in practice.
The safety of TRIPTODUR was evaluated in one uncontrolled, open-label single-arm clinical trial in which 44 children with central precocious puberty received two doses of TRIPTODUR and were observed for 12 months. The median age of the study population was 8 years (range 2-9 years) at treatment start; 88.6% of subjects were female, 59.1% were White, 27.3% were Black and 4.5% were Asian. Table 1 shows all the adverse reactions that occurred in at least 2 patients (≥4.5%) during the open-label single-arm trial.
Table 1: Adverse Reactions1 Occurring in ≥ 2 Patients Treated with TRIPTODUR in an Open-Label Single-Arm Trial

Adverse Reactions | Number of Patients Reporting Event (%) (Total N=44)
Infections & Infestations
Bronchitis | 2 (4.5)
Gastroenteritis | 3 (6.8)
Influenza | 2 (4.5)
Nasopharyngitis | 6 (13.6)
Otitis externa | 2 (4.5)
Pharyngitis | 2 (4.5)
Sinusitis | 2 (4.5)
Upper respiratory tract infection | 4 (9.1)
Nervous System Disorders
Headache | 6 (13.6)
Reproductive System & Breast Disorders
Menstrual (Vaginal bleeding)^2 | 3 (7.7)
Respiratory, Thoracic & Mediastinal Disorder
Cough | 3 (6.8)
Vascular Disorders
Hot flush | 2 (4.5)

^1Injection site reactions are presented separately
^2Includes % of patients with vaginal bleeding or menstrual disorder (“menstrual cycle returned”) in 39 females out of N=44.

Other Selected Adverse Reactions:
Injection Site Reactions
Injection site reactions occurring in patients immediately and/or 2 hours after injection include pain (45%), redness (14%), pruritus (2.3%) and swelling (2.3%).
Psychiatric Disorders
Anxiety (2.3%) and mood altered (2.3%)

6.2 Post-marketing Experience

The following adverse reactions have been identified during post-approval use of triptorelin or GnRH agonists. Because these reactions are reported voluntarily from a population of uncertain size, it is not always possible to reliably estimate their frequency or establish a causal relationship to drug exposure.

Hypersensitivity Reactions:Anaphylactic shock, anaphylactoid reaction, angioedema, urticaria.

Cardiovascular:Hypertension.

Psychiatric:Emotional lability, such as crying, irritability, impatience, anger, and aggression .Depression, including rare reports of suicidal ideation and attempt. Many, but not all, of these patients had a history of psychiatric illness or other comorbidities with an increased risk of depression.

Nervous System:Convulsions ,pseudotumor cerebri (idiopathic intracranial hypertension)

Vision Disorders:Visual impairment, visual disturbance

Skin Reactions: erythema multiforme, bullous dermatitis, dermatitis exfoliative, drug reaction with eosinophilia and systemic symptoms, Stevens-Johnson syndrome and toxic epidermal necrolysis, and acute generalized exanthematous pustulosis

7 DRUG INTERACTIONS

7.1 Drug-Drug Interactions

Results of in vitro studies show that drug-drug interactions with triptorelin are unlikely [see Clinical Pharmacology (12.3)]. However, in the absence of relevant data and as a precaution, hyperprolactinemic drugs should not be used concomitantly with triptorelin since hyperprolactinemia reduces the number of pituitary GnRH receptors.

7.2 Drug-Laboratory Test Interactions

Administration of TRIPTODUR results in suppression of the pituitary-gonadal system.

The effect of TRIPTODUR on pituitary and gonadal function is expected to disappear within six to twelve months after treatment discontinuation. Therefore, diagnostic tests of pituitary gonadotropic and gonadal functions conducted during treatment or after discontinuation of treatment may be affected.

8 USE IN SPECIFIC POPULATIONS

8.1 Pregnancy

Risk Summary
TRIPTODUR is contraindicated in women who are pregnant [see Contraindications (4)] since expected hormonal changes that occur with TRIPTODUR treatment increase the risk for pregnancy loss. Available data with triptorelin use in pregnant women are insufficient to determine a drug-associated risk of adverse developmental outcomes. Based on mechanism of action in humans and findings of increased pregnancy loss in animal studies, TRIPTODUR may cause fetal harm when administered to pregnant women. Advise pregnant women of the potential risk to a fetus.
The estimated background risk of major birth defects and miscarriage for the indicated population is unknown. In the US general population, the estimated background risk of major birth defects and miscarriage in clinically recognized pregnancies is 2% - 4% and 15% -20%, respectively.
Data
Animal Data
In pregnant rats administered triptorelin at doses of 2, 10, and 100 mcg/kg/day during the period of organogenesis, maternal toxicity (decrease in body weight) and embryo-fetal toxicities (pre-implantation loss, increased resorption, and reduced number of viable fetuses) were observed at 100 mcg/kg, approximately 4 times the clinical dose based on body surface area. No embryonic and fetal developmental toxicities were observed in mice at doses up to 4 times the clinical dose. Teratogenic effects were not observed in viable fetuses in rats or mice.

8.2 Lactation

Risk Summary
There are no data on the presence of triptorelin in human milk, or the effects of the drug on the breastfed infant, or on milk production. The developmental and health benefits of breastfeeding should be considered along with the mother’s clinical need for TRIPTODUR and any potential adverse effects on the breastfed child from TRIPTODUR or from the underlying maternal condition

8.6 Renal Impairment

TRIPTODUR has not been studied in children with renal impairment. Adult subjects with renal impairment had higher exposure than young healthy adult males [see Clinical Pharmacology (12.3)].

8.4 Pediatric Use

The safety and effectiveness of TRIPTODUR have been established in pediatric patients 2 years of age and older based on a single-arm open-label study of 44 children 2-9 years of age with CPP [see Clinical Studies (14)] . The safety and effectiveness of TRIPTODUR have not been established in pediatric patients less than 2 years old.

8.7 Hepatic Impairment

TRIPTODUR has not been studied in children with hepatic impairment. Adult subjects with hepatic impairment had higher exposure than young healthy adult males [see Clinical Pharmacology (12.3)].

10 OVERDOSAGE

There is no experience with overdosage in clinical trials of triptorelin. If overdosage occurs, therapy should be discontinued and appropriate supportive and symptomatic treatment administered.

11 DESCRIPTION

TRIPTODUR contains the pamoate salt of triptorelin, a synthetic decapeptide analog of naturally occurring gonadotropin-releasing hormone (GnRH or LHRH). The chemical name of triptorelin pamoate is 5-oxo-L-prolyl-L-histidyl-L-tryptophyl-L-seryl-L-tyrosyl-D-tryptophyl-L-leucyl-L-arginyl-L-prolylglycine amide (pamoate salt). The molecular weight is 1699.9 and the structural formula is:

TRIPTODUR for extended release injectable suspension for intramuscular use is provided as a sterile, lyophilized, biodegradable microgranule formulation in a single-dose vial, co-packaged with a syringe containing 2 mL Sterile Water for Injection for reconstitution of the lyophilisate. The triptorelin formulation is comprised of 22.5 mg triptorelin (equivalent to 31 mg triptorelin pamoate), carboxymethylcellulose sodium (26 mg), mannitol (74 mg), poly- d,l-lactide-co-glycolide (183 mg), and polysorbate 80 (1.7 mg). When 2 mL Sterile Water for Injection is added to the vial containing TRIPTODUR and mixed, a suspension is formed which is intended as a single intramuscular injection.

12 CLINICAL PHARMACOLOGY

12.1 Mechanism of Action

Triptorelin is a GnRH agonist.

12.2 Pharmacodynamics

Following the first administration, there is a transient surge in circulating levels of LH, FSH, testosterone, and estradiol [see Warnings and Precautions (5.2)] . After chronic and continuous administration, by 4 weeks after initiation of therapy, a sustained decrease in LH and FSH secretion and marked reduction in sex steroids are observed.

12.3 Pharmacokinetics

Absorption
After an initial intramuscular TRIPTODUR 22.5 mg injection and a second 22.5 mg intramuscular injection 24 weeks later in children 2 to 9 years old with CPP, triptorelin peaked 4 hours postdose with a geometric mean Cmax of 39.9 and 36.5 ng/mL, respectively. No apparent accumulation of triptorelin occurred after the second injection. Absorption occurred in two phases, a burst phase followed by a maintenance release phase. In children with CPP, following the burst phase after the first 22.5 mg injection, geometric mean serum triptorelin levels were 0.11, 0.17, 0.05 and 0.03 ng/mL at Months 1, 2, 3, and 6, respectively.
Distribution
There is no evidence that triptorelin, at clinically relevant concentrations, binds to plasma proteins.
Elimination
Metabolism
The metabolism of triptorelin in humans is unknown, but is unlikely to involve hepatic microsomal enzymes (cytochrome P450). Thus far no metabolites of triptorelin have been identified. Pharmacokinetic data suggest that C-terminal fragments produced by tissue degradation are either completely degraded in the tissues, or rapidly degraded in plasma, or cleared by the kidneys.
Excretion
Triptorelin is eliminated by both the liver and the kidneys. Following intravenous administration of 0.5 mg triptorelin peptide to six healthy male volunteers with a creatinine clearance of 149.9 mL/min, 41.7% of the dose was excreted in urine as intact peptide with a total triptorelin clearance of 211.9 mL/min. This percentage increased to 62.3% in patients with liver disease who have a lower creatinine clearance (89.9 mL/min). It has also been observed that the nonrenal clearance of triptorelin (patient anuric, Clcreat = 0) was 76.2 mL/min, thus indicating that the nonrenal elimination of triptorelin is mainly dependent on the liver.
Specific Populations
Renal Impairment
After intravenous bolus injection of 0.5 mg triptorelin in adults, the two distribution half-lives were unaffected by renal impairment. However, renal insufficiency led to a decrease in total triptorelin clearance proportional to the decrease in creatinine clearance as well as increases in volume of distribution and consequently, an increase in the elimination half-life. Adult male subjects with moderate or severe renal impairment had approximately 2-fold higher exposure (AUC values) than young healthy adult males (see Table 1) [see Use in Specific Populations (8.6)].
Hepatic Impairment
After intravenous bolus injection of 0.5 mg triptorelin in adults, the two distribution half-lives were unaffected by hepatic impairment. In adult males with hepatic insufficiency, triptorelin clearance was reduced and exposure (AUC) was increased 3.7-fold compared to young healthy adult males (Table 2) [see Use in Specific Populations (8.7)].
Table 2: Pharmacokinetic Parameters (Mean ± SD) in Healthy Adults, Adults with Renal Impairment, and Adults with Hepatic Impairment Following an I.V. Bolus of 0.5 mg Triptorelin in Solution

Group | Cmax (ng/mL) | AUCinf (h·ng/mL) | Clp (mL/min) | Clrenal (mL/min) | t1/2(h) | Clcreat (mL/min)
6 healthy male volunteers | 48.2 ±11.8 | 36.1 ±5.8 | 211.9 ±31.6 | 90.6 ±35.3 | 2.81 ±1.21 | 149.9 ±7.3
6 males with moderate renal impairment | 45.6 ±20.5 | 69.9 ±24.6 | 120.0 ±45.0 | 23.3 ±17.6 | 6.56 ±1.25 | 39.7 ±22.5
6 males with severe renal impairment | 46.5 ±14.0 | 88.0 ±18.4 | 88.6 ±19.7 | 4.3 ±2.9 | 7.65 ±1.25 | 8.9 ±6.0
6 males with liver disease | 54.1 ±5.3 | 131.9 ±18.1 | 57.8 ±8.0 | 35.9 ±5.0 | 7.58 ±1.17 | 89.9 ±15.1

Drug-Drug Interactions
In Vitro Assessment of Drug Interactions
Drug Metabolizing Enzyme Inhibition
Triptorelin did not inhibit CYP1A2, 2B6, 2C8, 2C9, 2C19 or 2D6, or CYP 3A4/5 at clinically relevant concentrations.
Drug Metabolizing Enzyme Induction
In fresh human hepatocytes from three human donors, triptorelin did not induce CYP1A2 or CYP3A4/5 activity.
Transporters
Triptorelin was a poor P-gp substrate and had no inhibitory effect toward P-gp.

13 NONCLINICAL TOXICOLOGY

13.1 Carcinogenesis, Mutagenesis, Impairment of Fertility

Carcinogenesis was evaluated in an 18-month study in mice and a 24-month study in rats. In rats, triptorelin doses of 120, 600, and 3000 mcg/kg given every 28 days (approximately 0.2, 0.8, and 4 times the estimated human monthly dose based on body surface area) resulted in increased mortality with a drug treatment period of 13 to 19 months. The incidences of benign and malignant pituitary tumors and histosarcomas were increased in a dose-related manner. There were no treatment-related tumors in mice at exposure up to 4-fold higher than the estimated human monthly dose based on body surface area.

Mutagenicity studies performed with triptorelin using bacterial and mammalian systems (in vitroAmes test and chromosomal aberration test in CHO cells and an in vivomouse micronucleus test) provided no evidence of mutagenic potential.

After 60 days of subcutaneous treatment followed by a minimum of four estrus cycles prior to mating, triptorelin at doses of 2, 20, and 200 mcg/kg (approximately 0.07, 0.7, and 7 times the estimated human daily dose based on body surface area) or two monthly injections as slow release microspheres (~20 mcg/kg/day) had no effect on the fertility or general reproductive function of female rats.

No studies were conducted to assess the effect of triptorelin on male fertility.

14 CLINICAL STUDIES

In a single-arm open-label study, 44 children 2 to 9 years of age with CPP, 39 females and 5 males, all naïve to previous GnRH agonist treatment, were administered TRIPTODUR 22.5 mg at a dosing interval of 24 weeks. Subjects were evaluated over two dosing intervals for a total of 12 months.

TRIPTODUR 22.5 mg suppressed pituitary release of LH and FSH and, consequently, gonadal secretion of estradiol in girls and testosterone in boys (Table 3). At all timepoints evaluated, ≥93% of children achieved LH suppression to prepubertal levels (i.e., serum LH ≤5 IU/L 30 minutes after GnRH agonist stimulation), ≥79% of girls achieved prepubertal levels of estradiol (i.e., <20 pg/mL), and ≥80% of boys achieved prepubertal levels of testosterone (i.e., <30 ng/dL). TRIPTODUR arrested or reversed progression of clinical signs of puberty with 95% of children showing no increase in the bone age/chronological age ratio, and 89% showing stabilization of sexual maturation at Month 12.

Table 3: Efficacy of TRIPTODUR 22.5 mg Administered Every 6 Months to Children with CPPa

Endpoint | % (n/N) of Children Achieving Endpoint
Endpoint | Month 1 | Month 2 | Month 3 | Month 6 | Month 9 | Month 12
% with prepubertal LH (GnRH-stim LH ≤5 IU/L) | 95% (42/44) | 95% (42/44) | 95% (42/44) | 93%b (41/44) | 95% (42/44) | 98% (43/44)
% girls with prepubertal estradiol (<20 pg/mL) | 87% (34/39) | 89% (34/38) | 92% (36/39) | 79% (31/39) | 82% (32/39) | 79% (31/39)
% boys with prepubertal testosterone (<30 ng/dL) | 80% (4/5) | 80% (4/5) | 100% (5/5) | 100% (5/5) | 80% (4/5) | 80% (4/5)
% with no increase in BA/CAc ratio vs. baseline |  |  |  | 64% (28/44) |  | 95% (42/44)
% achieving stabilization of sexual maturation |  |  |  | 91% (40/44) |  | 89% (39/44)
% girls with regression of uterine length |  |  |  | 69% (27/39) |  | 77% (30/39)
% boys with no progression in testis volumes |  |  |  | 100% (5/5) |  | 100% (5/5)

a-Intent-to-Treat population

b-Primary efficacy endpoint

c-Bone Age/Chronological Age

Following the second TRIPTODUR injection, 22 children (all girls) were assessed for evidence of an acute-on-chronic phenomenon (i.e., increase in basal LH >5 IU/L or serum estradiol level >20 pg/mL 48 hours after the second triptorelin injection). Of these, one girl who achieved prepubertal hormone levels prior to the second injection showed biochemical evidence of acute-on-chronic phenomenon [see Warnings and Precautions(5.2) and Adverse Reactions (6.1)].

16 HOW SUPPLIED/STORAGE AND HANDLING

Each TRIPTODUR 22.5 mg single-use kit (NDC 24338-150-20) contains:

- One single-dose vial of TRIPTODUR 22.5 mg (NDC 24338-150-01) with a Flip-Off seal containing sterile lyophilized white to slightly yellow powder cake
- One sterile, glass syringe with Luer Lock prefilled with 2 mL of Sterile Water for Injection (NDC 24338-150-02)
- Two sterile 21 gauge, 1½" needles (thin-wall) with safety cover
- One Package Insert

Store at 20 to 25°C (68 to 77°F) excursions permitted to 15°C to 30°C (59°F to 86°F) [see USP Controlled Room Temperature]. Do not freeze.

17 PATIENT COUNSELING INFORMATION

Advise the patient to read the FDA-approved patient labeling (Patient Information and Medication Guide).
Hypersensitivity Reactions
Inform caregivers that anaphylactic shock, hypersensitivity, and angioedema have been reported with triptorelin use and to immediately seek medical attention if any hypersensitivity reaction occurs.

Symptoms after Initial TRIPTODUR Administration
Inform caregivers that during the first weeks after the first TRIPTODUR injection, signs of puberty may occur such as vaginal bleeding [see Warnings and Precautions (5.1) and Adverse Reactions (6.1)]. Caregivers should notify the physician if these symptoms continue beyond the second month after TRIPTODUR administration.
Psychiatric Events
Inform caregivers that symptoms of emotional lability, such as crying, irritability, impatience, anger, and aggression have been observed in patients receiving GnRH agonists, including triptorelin. Alert caregivers to the possibility of development or worsening of psychiatric symptoms, including depression, during treatment with TRIPTODUR [see Warnings and Precautions (5.2) and Adverse Reactions (6.2)].
Convulsions
Inform caregivers that reports of convulsions have been observed in patients receiving GnRH agonists, including triptorelin. Patients with a history of seizures, epilepsy, cerebrovascular disorders, central nervous system anomalies or tumors, and patients on concomitant medications that have been associated with convulsions may be at increased risk [see Warnings and Precautions (5.3)].
Severe Cutaneous Adverse Reactions
Inform patients and/or caregivers that severe cutaneous adverse reactions (SCARs) may occur during treatment with TRIPTODUR. Advise patients and/or caregivers to stop TRIPTODUR and immediately contact their healthcare provider if they experience signs or symptoms of SCARs [see Warnings and Precautions (5.4)].
Pseudotumor Cerebri (Idiopathic Intracranial Hypertension)
Inform patients and caregivers that reports of pseudotumor cerebri (idiopathic intracranial hypertension) have been observed in pediatric patients receiving GnRH agonists, including triptorelin. Monitor patients for signs and symptoms of pseudotumor cerebri, including headache, and vision issues such as blurred vision, double vision, loss of vision, pain behind the eye or pain with eye movement, ringing in the ears, dizziness, and nausea. Advise patients and caregivers to contact their healthcare provider if the patient develops any of these symptoms. [see Warnings and Precautions (5.5)].
Pregnancy is Contraindicated
TRIPTODUR is contraindicated in pregnancy. If the patient becomes pregnant while taking the drug, the patient should be informed of the potential risk to fetus [see Use in Specific Populations (8.1)].
Compliance with the Dosing Schedule
Inform caregivers about the importance of adherence to the TRIPTODUR dosing schedule of one injection every 24 weeks. Patients should not miss or delay a scheduled dose.

Manufactured for:
Azurity Pharmaceuticals, Inc.
Woburn, MA 01801
Manufactured by:
Debiopharm Research & Manufacturing SA
CH-1920 Martigny, Switzerland
TRIPTODUR is a registered trademark of Debiopharm International SA.
Patent: https://azurity.com/patents_and_trademarks/
This product's labeling may have been updated. For current Full Prescribing Information, please visit www.triptodur.com
TRIP-PI-09 Rev. 09/2025

MEDICATION GUIDE

TRIPTODUR® [TRIP-toe-der]
(triptorelin)
for extended-release injectable suspension, for intramuscular use

What is the most important information I should know about TRIPTODUR?

- In the first few weeks after your child receives their first TRIPTODUR injection or after additional injections, TRIPTODUR can cause a brief increase in some hormones. During this time you may notice more signs of puberty in your child, including vaginal bleeding. Call your child’s doctor if signs of puberty continue after 2 months of receiving TRIPTODUR.
- Some people taking gonadotropin releasing hormone (GnRH) agonists like TRIPTODUR have had new or worsened mental (psychiatric) problems. Mental (psychiatric) problems may include emotional symptoms such as:
  - crying
  - irritability
  - restlessness (impatience)
  - anger
  - acting aggressive

Call your child’s doctor right away if your child has any new or worsening emotional symptoms while taking TRIPTODUR.

- Some people taking GnRH agonists like TRIPTODUR have had seizures. The risk of seizures may be higher in people who:
  - have a history of seizures
  - have a history of epilepsy
  - have a history of brain or brain vessel (cerebrovascular) problems or tumors
  - are taking a medicine that has been connected with seizures such as bupropion or selective serotonin reuptake inhibitors (SSRIs)

Seizures have also happened in people who have not had any of these problems.
Call your child’s doctor right away if your child has a seizure while taking TRIPTODUR.

- Severe cutaneous (skin) adverse reactions can happen during treatment with GnRH agonists like TRIPTODUR.
  Stop TRIPTODUR and call your child’s doctor right away if your child has any of the following signs or symptoms during treatment with TRIPTODUR:
  - skin rash or acnedry skin
  - itching
  - blisters on your skin
  - redness or swelling of your face, hands, or soles of your feet
  - blisters or sores in your mouth
  - peeling of your skin
  - fever
  - muscle or joint aches
  - swollen glands

Increased pressure in the fluid around the brain can happen in children taking GnRH agonists
medicines including TRIPTODUR.

- Call your child’s doctor right away if your child has any of the following symptoms during
  treatment with TRIPTODUR:
  - headache
  - ringing in the ears
  - eye problems, including blurred vision, double vision and decreased eyesight
  - dizziness
  - nausea
  - eye pain

What is TRIPTODUR?

- TRIPTODUR is an injectable prescription GnRH medicine used for the treatment of children with central precocious puberty (CPP).
- It is not known if TRIPTODUR is safe and effective in children under 2 years of age.

TRIPTODUR should not be taken if your child is:

- allergic to gonadotropin releasing hormone (GnRH), GnRH agonist medicines, or any ingredients in TRIPTODUR. See the end of this Medication Guide for a complete list of ingredients in TRIPTODUR.
- Some people taking triptorelin, the active ingredient in TRIPTODUR, have had serious allergic reactions. Call your child’s doctor or get emergency medical help right away if your child gets any of the following symptoms of a serious allergic reaction:
  - skin rashes, redness, or swelling
  - severe itching
  - hives
  - trouble breathing or swallowing
  - fast heart beat
  - sweating
  - throat tightness, hoarseness
  - swelling of face, mouth, and tongue
  - dizziness or fainting
- pregnant or becomes pregnant. TRIPTODUR can cause birth defects or loss of the baby. If your
  child becomes pregnant call your doctor.

Before your child receives TRIPTODUR, tell your child’s doctor about all of your child’s medical conditions, including if they:

- have a history of mental (psychiatric) problems.
- have a history of seizures.
- have a history of epilepsy.
- have a history of brain or brain vessel (cerebrovascular) problems or tumors.
- are breastfeeding or plan to breastfeed. It is not known if TRIPTODUR passes into breastmilk.

Tell the doctor about all the medicines your child takes, including prescription and over-the-counter medicines, vitamins, and herbal supplements.

How will your child receive TRIPTODUR?

- Your child’s doctor should do tests to make sure your child has CPP before treating them with TRIPTODUR.
- TRIPTODUR must only be given by a healthcare professional.
- TRIPTODUR is given as a single intramuscular (in the muscle) injection 1 time every 24 weeks.
- Keep all scheduled visits to the doctor. Do not delay a scheduled dose. The doctor will do regular exams and blood tests to check for signs of puberty.

What are the possible side effects of TRIPTODUR?
TRIPTODUR may cause serious side effects. See “What is the most important information I should know about TRIPTODUR?”
The most common side effects of TRIPTODUR include injection site reactions, menstrual (vaginal) bleeding, hot flush, headache, cough, and infections (bronchitis, gastroenteritis, influenza, nasopharyngitis, otitis externa, pharyngitis, sinusitis, and upper respiratory tract infection).
These are not all the possible side effects of TRIPTODUR. Call your doctor for medical advice about side effects. You may report side effects to FDA at 1-800-FDA-1088.

What are the ingredients in TRIPTODUR?
Active ingredient: triptorelin
Inactive ingredients: carboxymethylcellulose sodium, mannitol, poly-d,l-lactide-co-glycolide, and polysorbate 80
Distributed by: Azurity Pharmaceuticals, Inc. Woburn, MA 01801
Manufactured by: Debiopharm Research & Manufacturing SA, CH-1920 Martigny, Switzerland
For more information about TRIPTODUR, please contact Azurity Pharmaceuticals, Inc. at 1-800-461-7449.

This Medication Guide has been approved by the U.S. Food and Drug Administration Rev: 09/2025
TRIPTODUR is a registered trademark of Debiopharm International SA.
TRIP-MG-07

PRINCIPAL DISPLAY PANEL - Kit Carton

NDC 24338-150-20
Rx Only

Triptodur ®
(triptorelin)
for extended-release injectable suspension

22.5 mg

KIT
22.5 mg every 24 weeks

FOR INTRAMUSCULAR USE

Must only be administered by a healthcare professional.

Give once every 24 weeks.
Single-Dose Delivery System
See package insert for full prescribing information.

Contents:

–One Single-Dose Vial

–One Pre-filled Syringe of Diluent (sterile water) for Triptodur, 2 mL

–Two thin-walled, 21-gauge, 1½" Needles

Reconstitute With Accompanying Diluent Before Use.

After reconstitution, ensure there are no visible precipitates in the vial and administer immediately.

Dispense the accompanying Medication Guide to each patient.

azurity ® pharmaceuticals